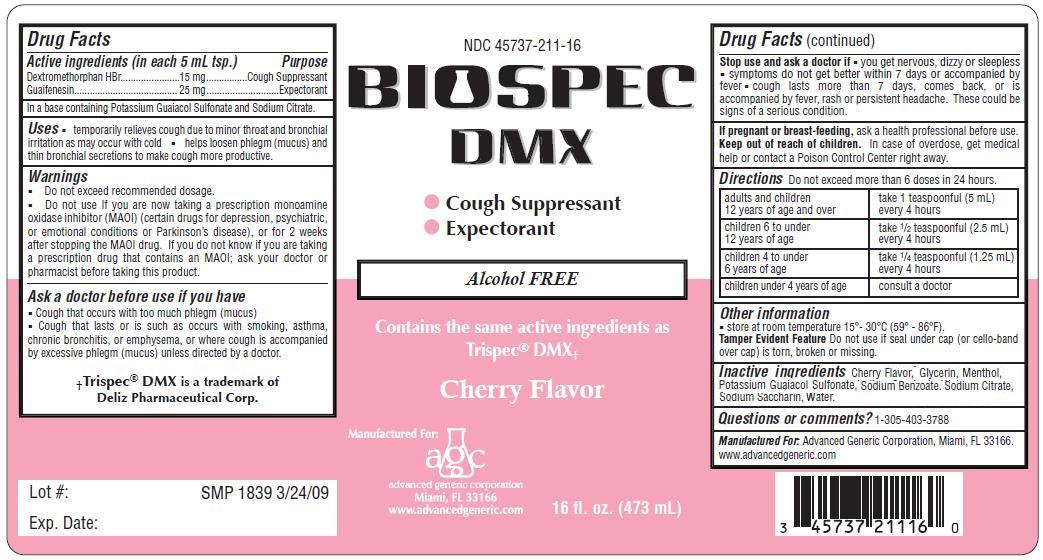 DRUG LABEL: Biospec
NDC: 45737-211 | Form: LIQUID
Manufacturer: Advanced Generic Corporation
Category: otc | Type: HUMAN OTC DRUG LABEL
Date: 20241220

ACTIVE INGREDIENTS: DEXTROMETHORPHAN HYDROBROMIDE 15 mg/5 mL; GUAIFENESIN 25 mg/5 mL
INACTIVE INGREDIENTS: MENTHOL; WATER; POTASSIUM GUAIACOLSULFONATE; GLYCERIN; SODIUM BENZOATE; SODIUM CITRATE; SACCHARIN SODIUM

AGC-BiospecDMX 211

Active Ingredients: (in each 5 mL tsp.) Purpose
Dextromethorphan Hydrobromide 15 mg.................. Cough Suppressant
Guaifenesin 25 mg .............................................. Expectorant

Uses

- temporarily relieves cough due to minor throat and bronchial irritations as may occur with a cold

- helps loosen phlegm (mucus) and thin bronchial secretions to make coughs more productive

Warnings

- Do not exceed recommended dosage.

- Do not use If you are now taking a prescription monoamine oxidase inhibitor (MAOI) (certain drugs for depression, psychiatric, or emotional conditions or Parkinson’s disease), or for 2 weeks after stopping the MAOI drug. If you do not know if you are taking a prescription drug that contains an MAOI; ask your doctor or pharmacist before taking this product.

Ask a doctor before use if you have

- Cough that occurs with too much phlegm (mucus)

- Cough that lasts or is such as occurs with smoking, asthma, chronic bronchitis, or emphysema, or where cough is accompanied by excessive phlegm (mucus) unless directed by a doctor.

Stop use and ask a doctor if

- you get nervous, dizzy or sleepless
- symptoms do not get better within 7 days or accompanied by fever
- cough lasts more than 7 days, comes back, or is accompanied by fever, rash or persistent headache. These could be signs of a serious condition.

PREGNANCY OR BREAST FEEDING

If pregnant or breast-feeding,ask a health professional before use.

Keep out of reach of children.

DOSAGE AND ADMINISTRATION

DirectionsDo not take more than 6 doses in any 24-hour period, unless directed by a physician

adults and children 12 years and over, 1 teaspoonfuls (5 ml) every 4 hours

children 6 years to under 12 years, 1/2 teaspoonful (2.5 ml) every 4 hours

children 4 to 6 years, 1/4 teaspoonful (1.25 ml) every 4 hours

children under 4 years of age, consult a doctor

INDICATIONS AND USAGE

Other informationstore at room temperature 15-30 C (59-86 F).

Tamper Evident FeatureDo not use if seal under cap (or cello-band over cap) is torn, broken or missing.

INACTIVE INGREDIENT

Inactive ingredientsCherry Flavor, Glycerin, Menthol, Potassium Guaiacol Sulfonate,
Sodium Benzoate, Sodium Citrate, Sodium Saccharin, Water.

Questions or comments?1-305-403-3788
Manufactured For:Advanced Generic Corporation, Miami, FL 33166.
www.advancedgeneric.com